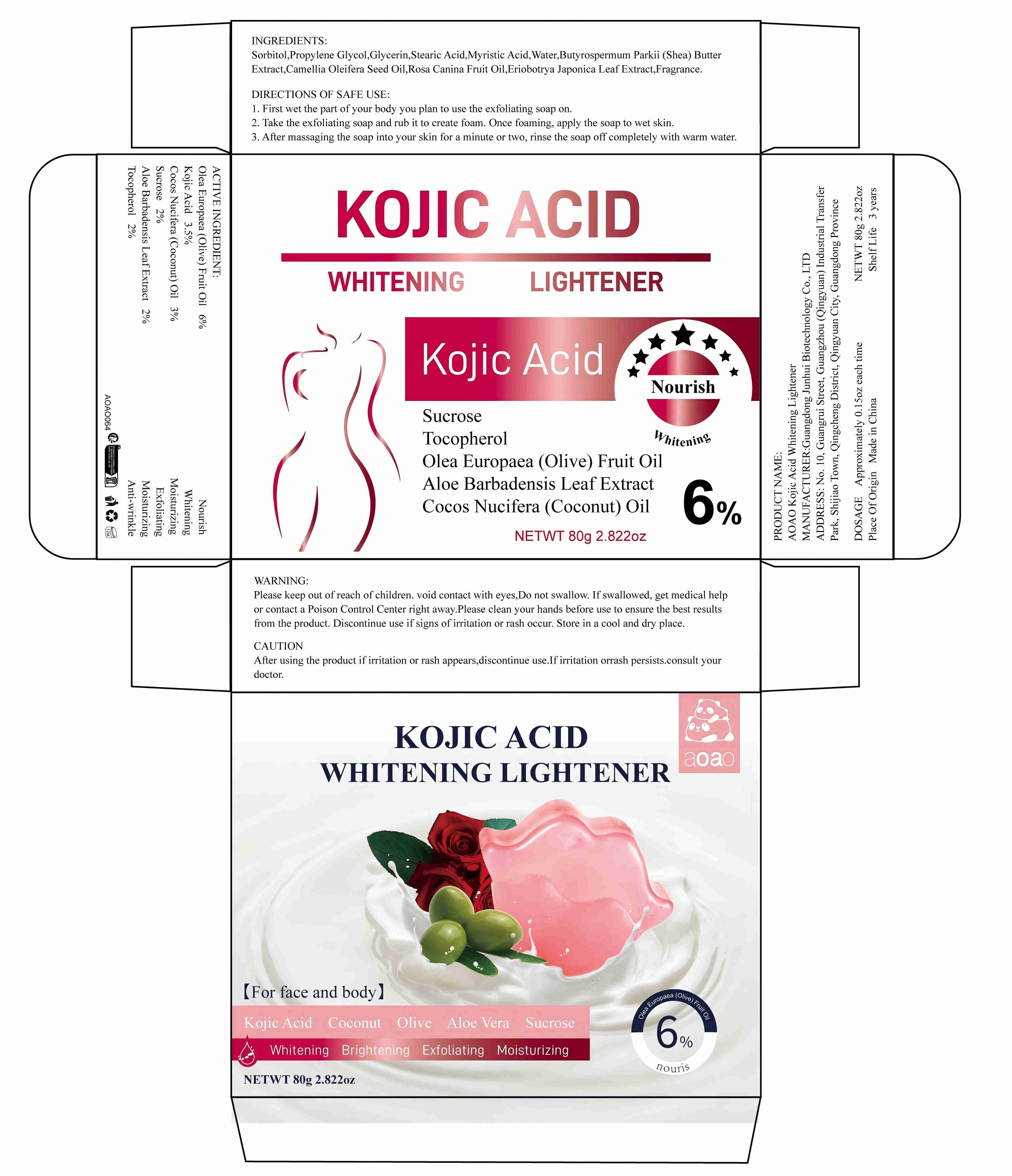 DRUG LABEL: AOAO Kojic Acid Whitening Lightener
NDC: 84509-035 | Form: SOAP
Manufacturer: Guangdong Junhui Biotechnology Co., LTD
Category: otc | Type: HUMAN OTC DRUG LABEL
Date: 20241029

ACTIVE INGREDIENTS: TOCOPHEROL 1600 mg/80 g; KOJIC ACID 3200 mg/80 g; COCOS NUCIFERA (COCONUT) OIL 2400 mg/80 g; ALOE BARBADENSIS LEAF EXTRACT 1600 mg/80 g; OLEA EUROPAEA (OLIVE) FRUIT OIL 4800 mg/80 g; SUCROSE 1600 mg/80 g
INACTIVE INGREDIENTS: MYRISTIC ACID; WATER; STEARIC ACID; ERIOBOTRYA JAPONICA LEAF EXTRACT; ROSA CANINA FRUIT OIL; CAMELLIA OLEIFERA SEED OIL; BUTYROSPERMUM PARKII (SHEA) BUTTER EXTRACT; PROPYLENE GLYCOL; FRAGRANCE 13576; SORBITOL; GLYCERIN

Active Ingredients

Olea Europaea (Olive) Fruit Oil 6%
Kojic Acid 4%
Cocos Nucifera (Coconut) Oil 3%
Sucrose 2%
Aloe Barbadensis Leaf Extract 2%
Tocopherol 2%

Purpose

Nourish
Whitening
Moisturizing
Exfoliating
Moisturizing
Anti-wrinkle

Uses

1. First wet the part of your body you plan to use the exfoliating soap on.
2. Take the exfoliating soap and rub it to create foam. Once foaming, apply the soap to wet skin.
3. After massaging the soap into your skin for a minute or two, rinse the soap off completely with warm water.

Inactive Ingredients

Sorbitol,Propylene Glycol,Glycerin,Stearic Acid,Myristic Acid， Water,Butyrospermum Parkii (Shea) Butter Extract,Camellia Oleifera Seed Oil,Rosa Canina Fruit Oil,Eriobotrya Japonica Leaf Extract,Fragrance

Product Name

AOAO Kojic Acid Whitening Lightener

Warnings

For external use only. Keep out ofreach of children.Avoid contact with eyes.

Keep out of reach of children

If swallowed, get medical help or contact a Poison Control Center right away

CAUTION

After using the product ifirritation or rash appears,discontinue use.Ifirritation or
rash persists.consult your doctor.

DOSAGE

Approximately 0.15oz each time

Manufacturer

Guangdong Junhui Biotechnology Co., LTD

ADDRESS

No. 10, Guangrui Street, Guangzhou (Qingyuan) Industrial Transfer Park, Shijiao Town, Qingcheng District, Qingyuan City, Guangdong Province

Capacity

80g 2.822oz

Shelf Life

3 Years

Place of Origin

Made in China